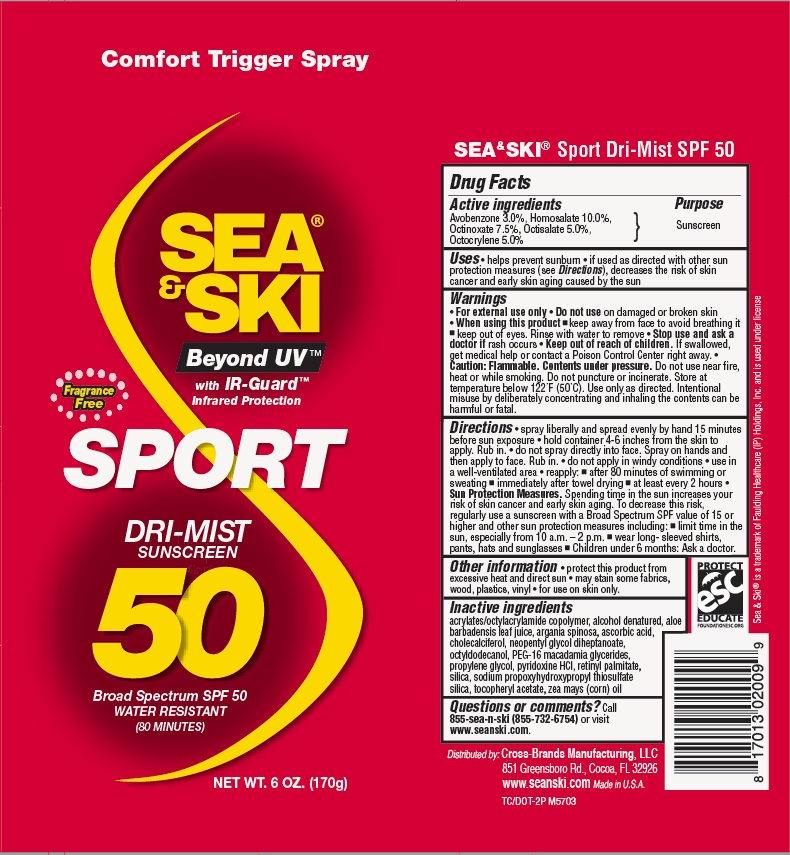 DRUG LABEL: General Protection
NDC: 73440-2009 | Form: AEROSOL, SPRAY
Manufacturer: Cross-Brands Contract Filling
Category: otc | Type: HUMAN OTC DRUG LABEL
Date: 20210326

ACTIVE INGREDIENTS: HOMOSALATE 17 g/170 g; AVOBENZONE 5.1 g/170 g; OCTINOXATE 12.75 g/170 g; OCTOCRYLENE 8.5 g/170 g; OCTISALATE 8.5 g/170 g
INACTIVE INGREDIENTS: ALCOHOL 107.61 g/170 g

Sea & Ski SPF 50 Sport CSpray